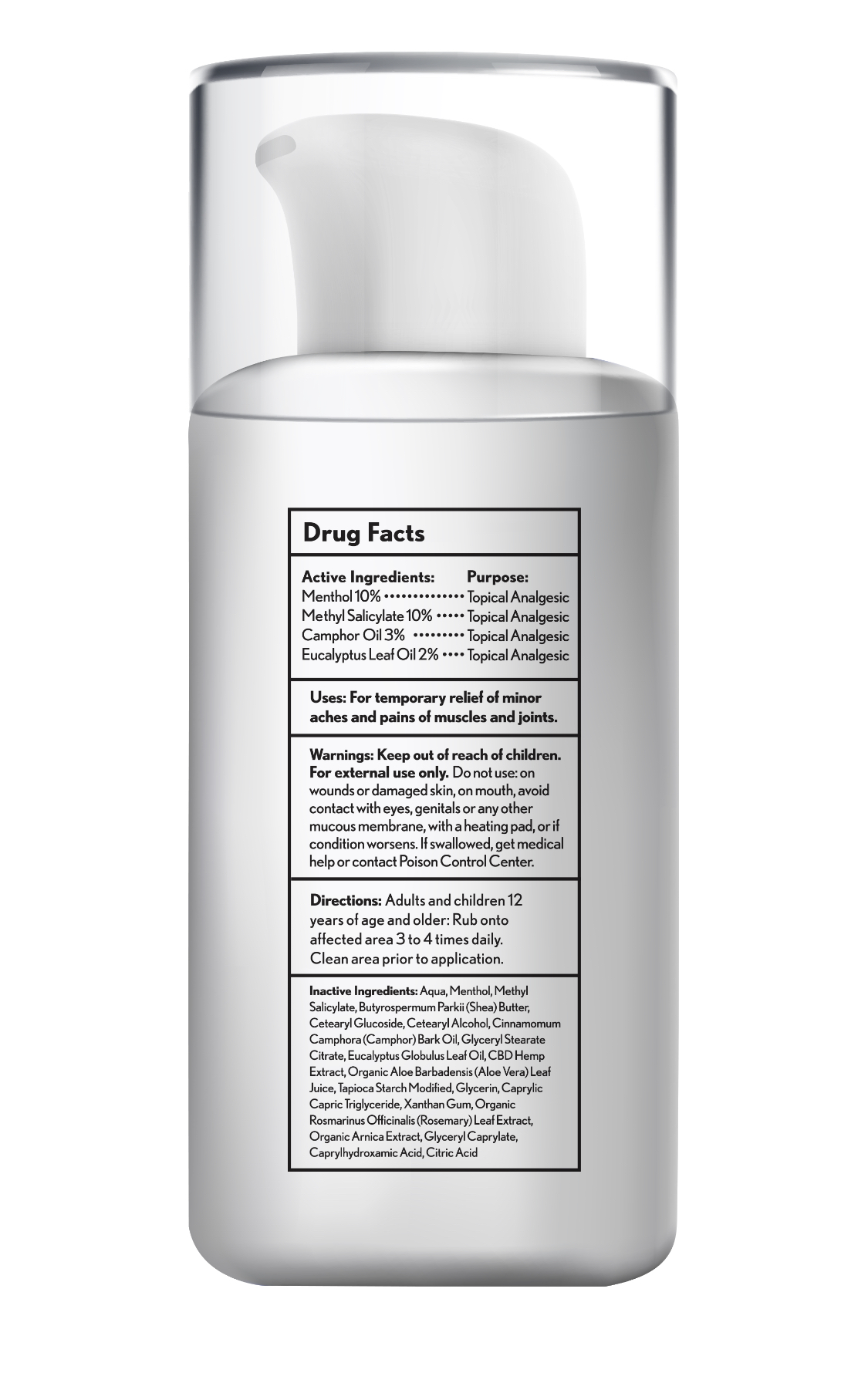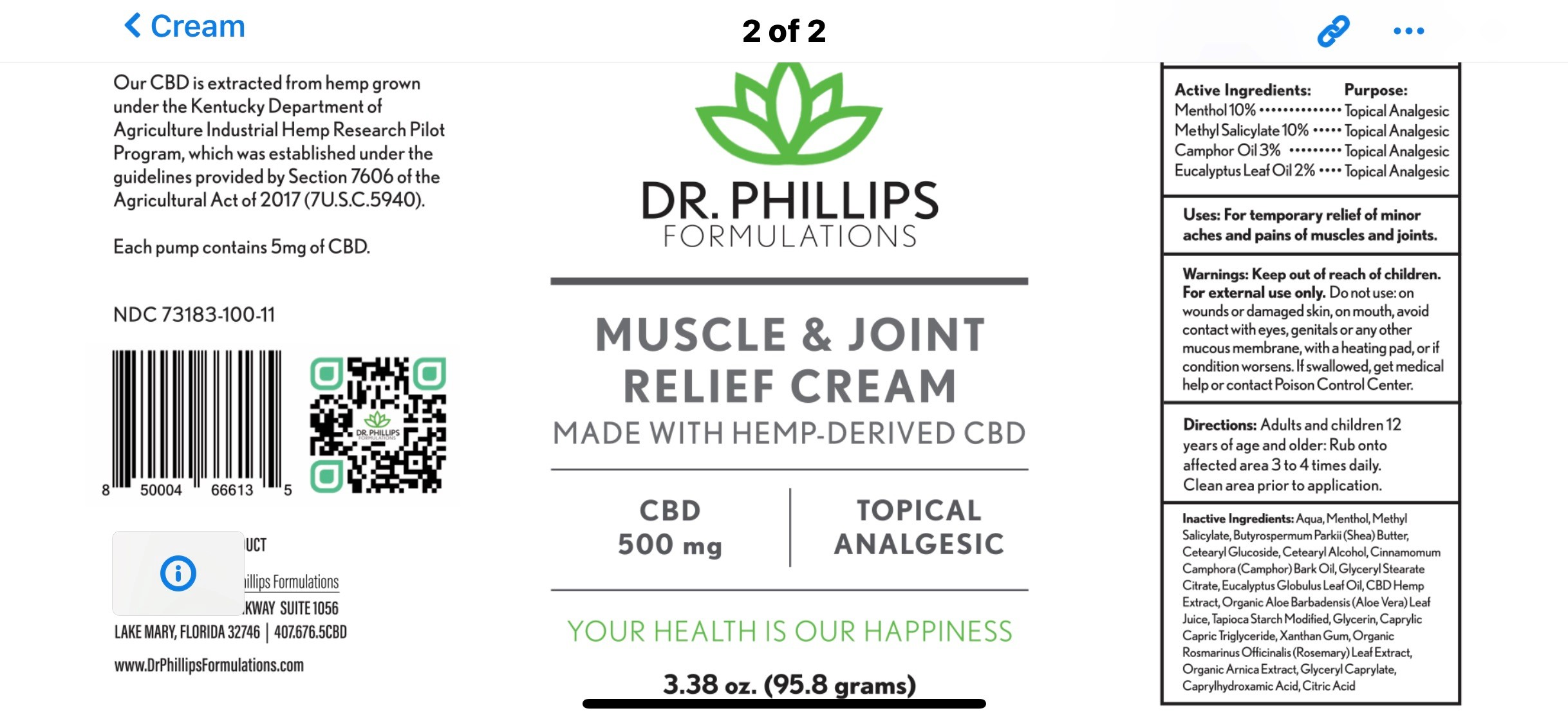 DRUG LABEL: Dr. Phillips Formulations Muscle Joint Relief
NDC: 73183-100 | Form: CREAM
Manufacturer: Dr. Phillips Formulations, LLC
Category: otc | Type: HUMAN OTC DRUG LABEL
Date: 20201229

ACTIVE INGREDIENTS: MENTHOL 10 mg/100 mg; METHYL SALICYLATE 10 mg/100 mg; EUCALYPTUS OIL 2 mg/100 mg; CAMPHOR (NATURAL) 3 mg/100 mg
INACTIVE INGREDIENTS: WATER; CETEARYL GLUCOSIDE; XANTHAN GUM; SHEA BUTTER

ACTIVE INGREDIENT

Menthol - 10%

Methyl Salicylate - 10%

Camphor Oil - 3%

Eucalyptus Oil - 2%

Keep out of reach of children

PURPOSE

For temporary relief of minor aches and pains of muscles and joints.

DOSAGE AND ADMINISTRATION

Rub onto affected area 3 to 4 times daily. Clean area prior to application.

Keep out of reach of children. For external use only. Do not use on wounds or damaged skin, on mouth, avoid contact with eyes, genitals or any other mucous membrane, with a heating pad, or if condition worsens. If swallowed, get medical help or contact Poison Control Center.

INDICATIONS AND USAGE

For temporary relief of minor aches and pains of muscles and joints.

INACTIVE INGREDIENT

Aqua, Butyrospermum Parkii (Shea) Butter, Cetearyl Glucoside, Cetearyl Alcohol, Cinnamomum Camphora, Glyceryl Stearate Citrate, CBD Hemp Extract, Prganic Aloe Barbadensis (Aloe Vera) leaf Juice, Tapioca Starch Modified, CLycerin, Caprylic, Capric Triglyceride, Xanthan Gum, Organic Rosmariun Officianalis (Rosemary) Leaf Extract, Organic Arnica Extract, Glyceryl Caprylate, Caprylhydroxamic Acid, Citric Acid